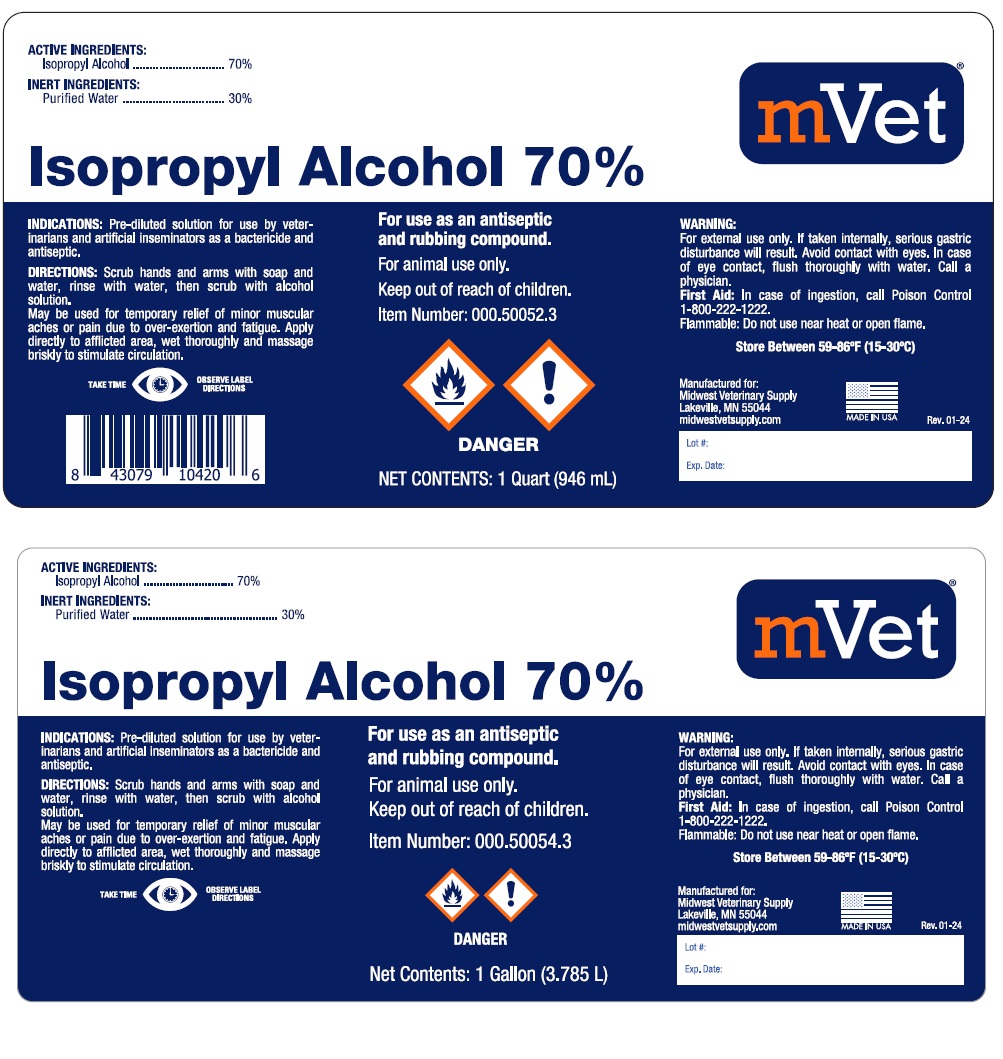 DRUG LABEL: ISOPROPYL ALCOHOL
NDC: 86223-032 | Form: LIQUID
Manufacturer: Midwest Veterinary Supply, Inc.
Category: animal | Type: OTC ANIMAL DRUG LABEL
Date: 20250508

ACTIVE INGREDIENTS: ISOPROPYL ALCOHOL 70 L/100 L
INACTIVE INGREDIENTS: WATER 30 L/100 L

WARNINGS AND PRECAUTIONS

Isopropyl Alcohol 70%

For use as an antiseptic and rubbing compound.

For animal use only

Keep out of reach of children.

ACTIVE INGREDIENTS:

Isopropyl Alcohol ................. 70%

INERT INGREDIENTS:

Purified Water ...................................30%

INDICATIONS: Pre-diluted solution for use by veterinarians and artificial inseminators as a bactericide and antiseptic.

DIRECTIONS: Scrub hands and arms with soap and water, rinse with water, then scrub with alcohol solution.

May be used for temporary relief of minor muscular aches or pain due to over-exertion and fatigue. Apply directly to affected area, wet thoroughly and massage briskly to stimulate circulation.

WARNING: For external use only. If taken internally, serious gastric disturbance will result. Avoid contact with eyes. In case of eye contact, flush thoroughly with water. Call a physician.

First Aid: In case of ingestion, call Poison Control 1-800-222-1222.

Flammable: Do not use near heat or open flames.

Store Between 59-86°F (15-30°C)

Manufactured for:

Midwest Veterinary Supply

Lakeville, MN 55044

midwestvetsupply.com

MADE IN USA